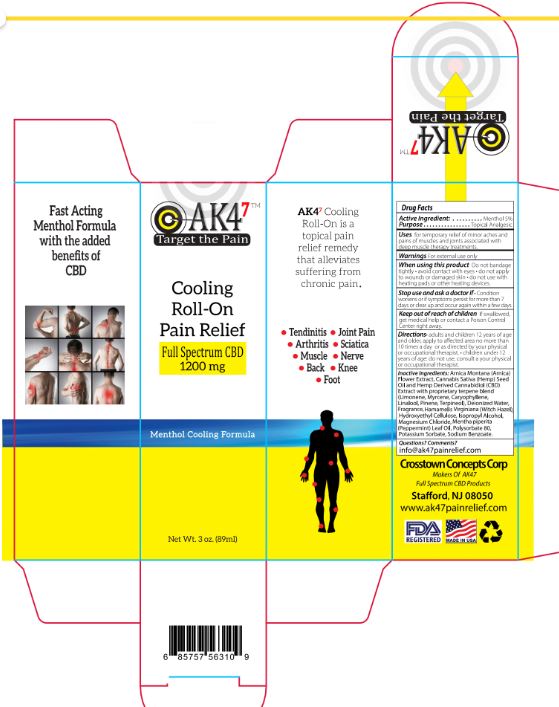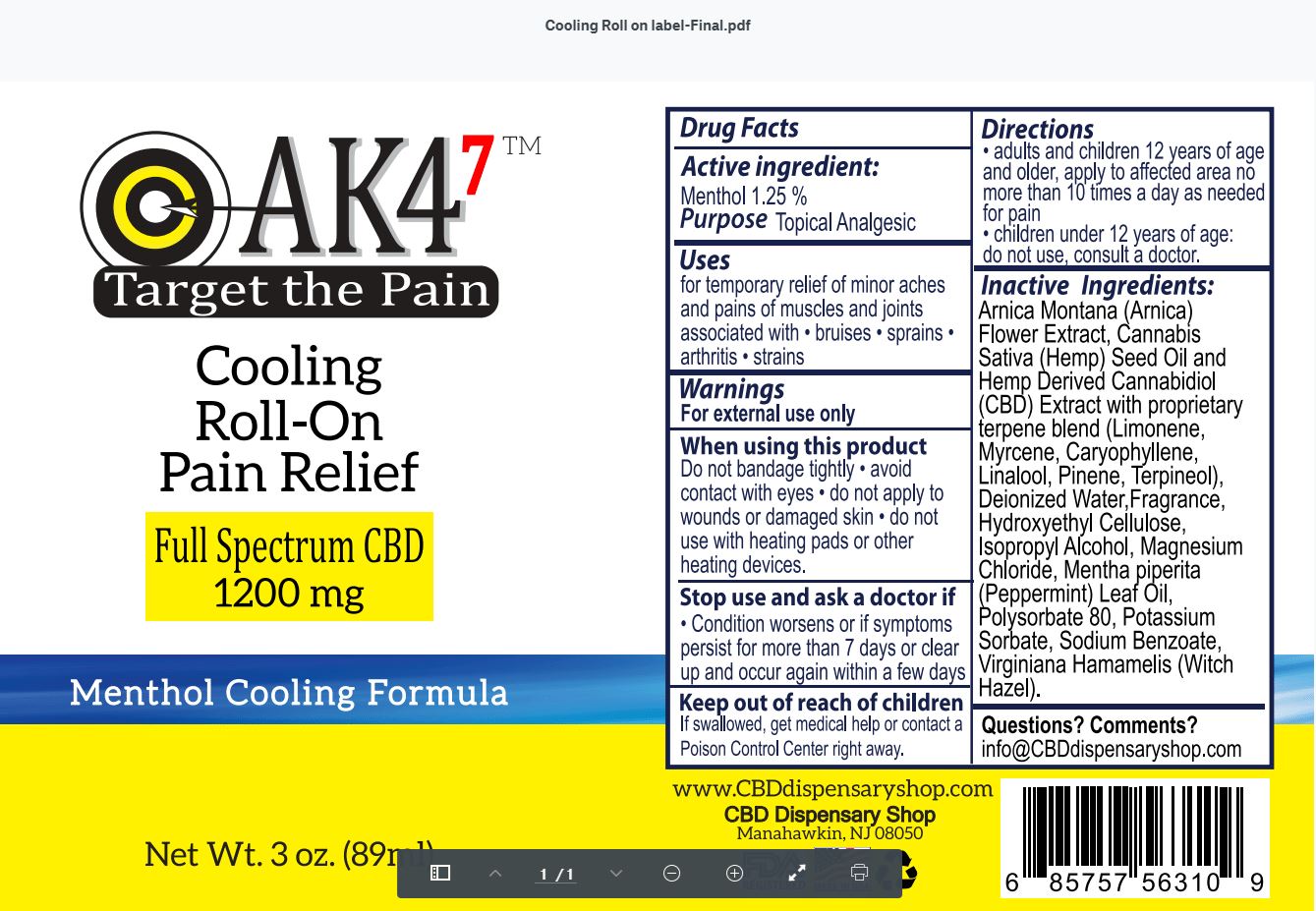 DRUG LABEL: AK47 Cooling Roll-On
NDC: 76348-570 | Form: LIQUID
Manufacturer: Renu Laboratories, Inc.
Category: otc | Type: HUMAN OTC DRUG LABEL
Date: 20200806

ACTIVE INGREDIENTS: MENTHOL 1.05 g/84 g
INACTIVE INGREDIENTS: TERPINEOL; CANNABIDIOL; MAGNESIUM CHLORIDE; PEPPERMINT OIL; POLYSORBATE 80; CARYOPHYLLENE; CANNABIS SATIVA SEED OIL; ISOPROPYL ALCOHOL; WITCH HAZEL; SODIUM BENZOATE; ARNICA MONTANA FLOWER; WATER; GRAPEFRUIT; POTASSIUM SORBATE; MYRCENE; HYDROXYETHYL CELLULOSE, UNSPECIFIED; LINALOOL, (+/-)-; .ALPHA.-PINENE, (+)-; LIMONENE, (+)-

AK4^7 Cooling Roll-On Pain Relief

Active ingredient: Menthol 1.25%

Purpose Topical Analgesic

Uses

for temporary relief of minor aches and pains of muscles and joints associated with

- bruises
- sprains
- arthritis
- strains

Warnings

For external use only.

When using this product

- Do not bandage tightly
- avoid contact with eyes
- do not apply to wounds or damaged skin
- do not use with heating pads or other heating devices.

Stop use and ask a doctor if

- Condition worsens or if symptoms persist for more than 7 days or clear up and occur again within a few days

Keep out of reach of children

If swallowed, get medical help or contact a Poison Control Center right away.

Directions

- Adults and children 12 years of age and older, apply to affected area no more than 10 times a day as needed for pain.
- children under 12 years of age: do not use, consult a doctor.

Inactive Ingredients:

Arnica Montana (Arnica) Flower Extract, Cannabis Sativa (Hemp) Seed Oil and Hemp Derived Cannabidiol (CBD) Extract with proprietary terpene blend (Limonene, Myrcene, Caryophyllene, Linalool, Pinene, Terpineol), Deionized Water, Fragrance, Hydroxyethyl Cellulose, Isopropyl Alcohol, Magnesium Chloride, Mentha piperita (Peppermint) Leaf Oil, Polysorbate 80, Potassium Sorbate, Sodium Benzoate, Virginiana Hamamelis (Witch Hazel).

Questions? Comments?

info@CBDdispensaryshop.com

STATEMENT OF IDENTITY

AK47 TM

Cooling Roll-On

Pain Relief

RECENT MAJOR CHANGES

USES CHANGED TO VARIOUS BULLET POINTS

5/2020

DOSAGE AND ADMINISTRATION

Changes made to Directions

5/2020

LABEL AND BOX

AK47 LABEL AND PRODUCT BOX